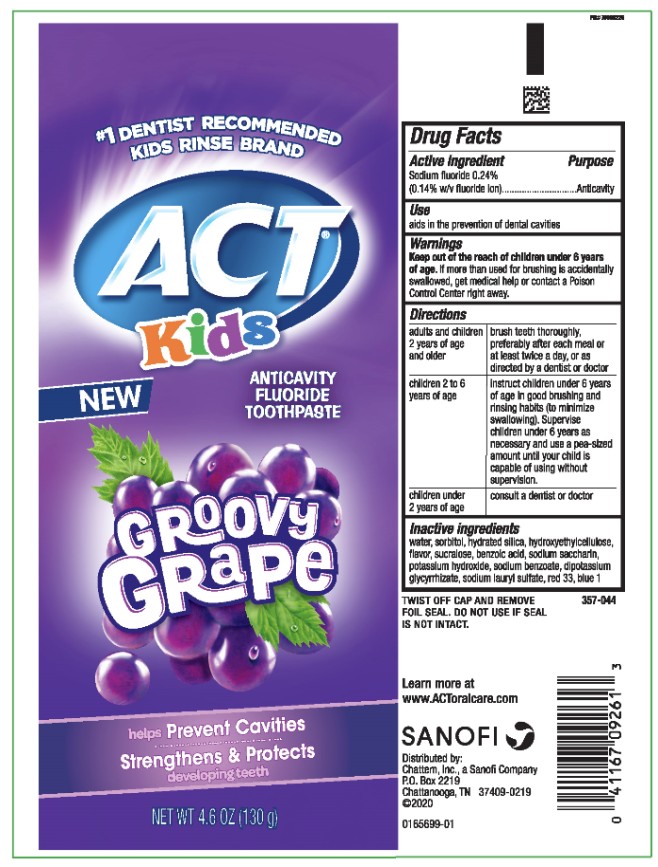 DRUG LABEL: ACT Kids Anticavity Fluoride Groovy Grape
NDC: 41167-0926 | Form: PASTE, DENTIFRICE
Manufacturer: Chattem, Inc.
Category: otc | Type: HUMAN OTC DRUG LABEL
Date: 20260112

ACTIVE INGREDIENTS: SODIUM FLUORIDE 1.4 mg/1 g
INACTIVE INGREDIENTS: WATER; SORBITOL; HYDRATED SILICA; HYDROXYETHYL CELLULOSE, UNSPECIFIED; SUCRALOSE; BENZOIC ACID; SACCHARIN SODIUM; POTASSIUM HYDROXIDE; SODIUM BENZOATE; GLYCYRRHIZINATE DIPOTASSIUM; SODIUM LAURYL SULFATE; D&C RED NO. 33; FD&C BLUE NO. 1

ACT Kids Anticavity Fluoride Toothpaste Groovy Grape

ACT Kids

Anticavity Fluoride Toothpaste

Groovy Grape

Drug Facts

Active ingredient

Sodium fluoride 0.24% (0.14% w/v fluoride ion)

Purpose

Anticavity

Use

aids in the prevention of dental cavities

Warnings

Keep out of the reach of children under 6 years of age.

If more than used for brushing is accidentally swallowed, get medical help or contact a Poison Control Center right away.

Directions

adults and children 2 years of age and older | brush teeth thoroughly, preferably after each meal or at least twice a day, or as directed by a dentist or doctor
children 2 to 6 years of age | instruct children under 6 years of age in good brushing and rinsing habits (to minimize swallowing). Supervise children under 6 years as necessary and use a pea-sized amount until your child is capable of using without supervision.
children under 2 years of age | consult a dentist or doctor

Inactive ingredients

water, sorbitol, hydrated silica, hydroxyethylcellulose, flavor, sucralose, benzoic acid, sodium saccharin, potassium hydroxide, sodium benzoate, dipotassium glycyrrhizate, sodium lauryl sulfate, red 33, blue 1

PRINCIPAL DISPLAY PANEL

ACT
Kids
NEW
ANTICAVITY
FLUORIDE
TOOTHPASTE
GROOVY
Grape
NET WT 4.6 OZ (130 g)